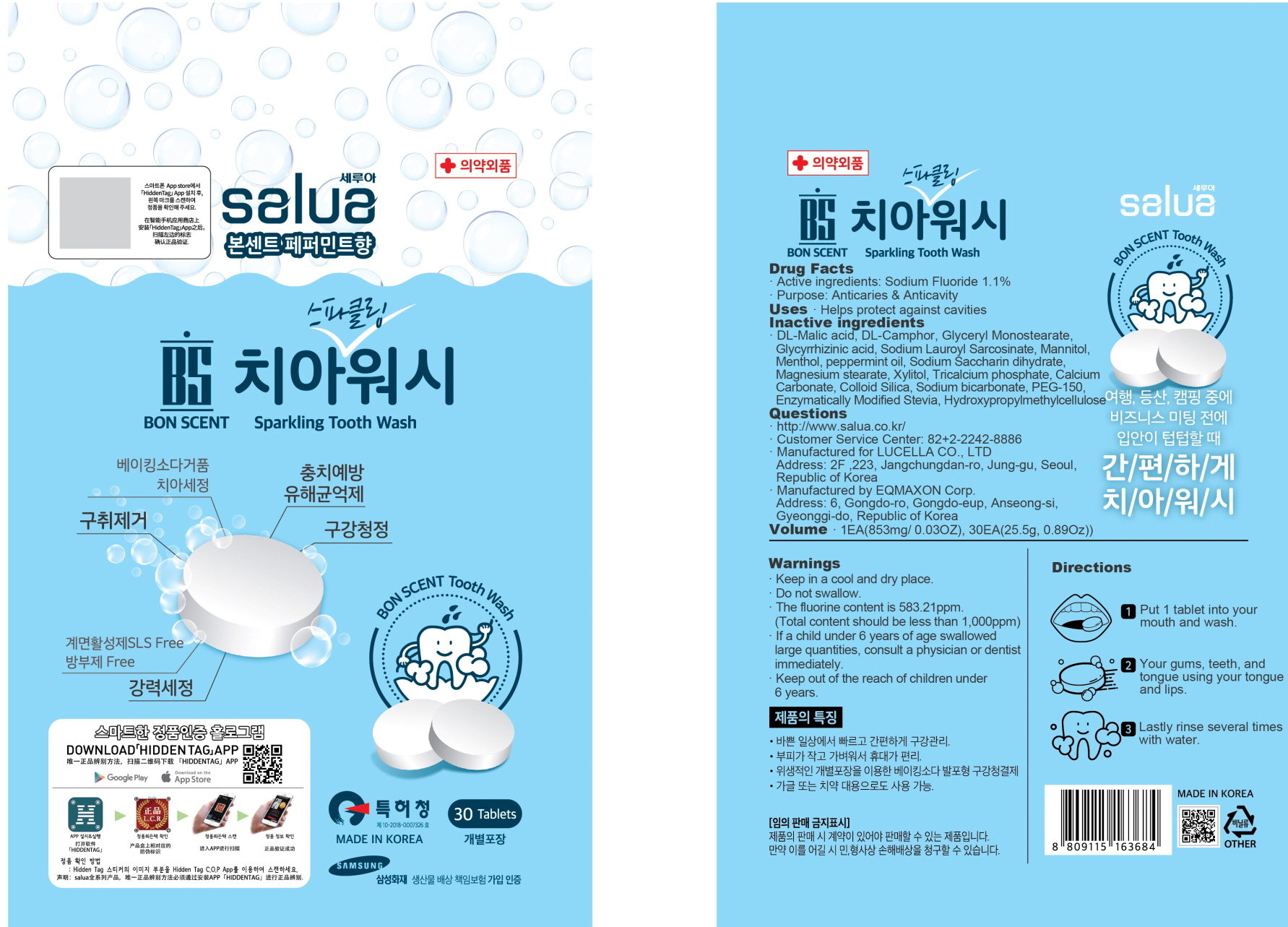 DRUG LABEL: BON SCENT Sparkling Tooth Wash
NDC: 72869-010 | Form: TABLET
Manufacturer: Lucella Co.,ltd
Category: otc | Type: HUMAN OTC DRUG LABEL
Date: 20190417

ACTIVE INGREDIENTS: Sodium Fluoride 9.38 mg/853 mg
INACTIVE INGREDIENTS: Mannitol; Menthol

ACTIVE INGREDIENT

Active ingredients: Sodium Fluoride 1.1%

INACTIVE INGREDIENT

Inactive ingredients:

DL-Malic acid, DL-Camphor, Glyceryl Monostearate, Glycyrrhizinic acid, Sodium Lauroyl Sarcosinate, Mannitol, Menthol, peppermint oil, Sodium Saccharin dihydrate, Magnesium stearate, Xylitol, Tricalcium phosphate, Calcium Carbonate, Colloid Silica, Sodium bicarbonate, PEG-150, Enzymatically Modified Stevia, Hydroxypropylmethylcellulose

PURPOSE

Purpose: Anticaries & Anticavity

WARNINGS

- Keep in a cool and dry place.
- Do not swallow.
- The fluorine content is 583.21ppm. (Total content should be less than 1,000ppm)
- If a child under 6 years of age swallowed large quantities, consult a physician or dentist immediately.
- Keep out of the reach of children under 6 years.

KEEP OUT OF REACH OF CHILDREN

Keep out of the reach of children under 6 years.

Uses

Helps protect against cavities

Directions

- Put 1 tablet into your mouth and wash your gums, teeth, and tongue using your tongue and lips.
-Lastly rinse several times with water.